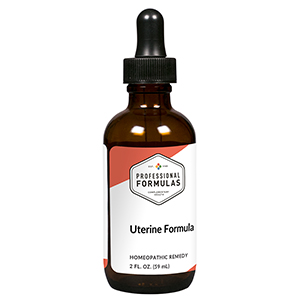 DRUG LABEL: Uterine Formula
NDC: 63083-2105 | Form: LIQUID
Manufacturer: Professional Complementary Health Formulas
Category: homeopathic | Type: HUMAN OTC DRUG LABEL
Date: 20190815

ACTIVE INGREDIENTS: LINDERA AGGREGATA ROOT 1 [hp_X]/59 mL; VITEX NEGUNDO FRUIT 1 [hp_X]/59 mL; ACONITUM CARMICHAELI LATERAL ROOT 3 [hp_X]/59 mL; CINNAMOMUM CASSIA TWIG 3 [hp_X]/59 mL; CROCUS SATIVUS FLOWER 3 [hp_X]/59 mL; PHELLODENDRON CHINENSIS BARK 3 [hp_X]/59 mL; CRASSOSTREA GIGAS SHELL 3 [hp_X]/59 mL; VISCUM ALBUM FRUITING TOP 3 [hp_X]/59 mL; ASTRAGALUS PROPINQUUS ROOT 6 [hp_X]/59 mL
INACTIVE INGREDIENTS: ALCOHOL; WATER

C105

ACTIVE INGREDIENTS

Wu-Yao 1X
Zi-Hua-Ti-Ting 1X
Fu-Tzu 3X
Gui-Zhi 3X
Hong-Hua 3X
Huang-Bo 3X
Mu-Li 3X
Sang-Ji-Sheng 3X
Huang-Qi 6X

QUESTIONS

Professional Formulas

PO Box 2034 Lake Oswego, OR 97035

INDICATIONS

For the temporary relief of painful or heavy menses, abdominal cramping, or aches in back or legs.*

PURPOSE

*Claims based on traditional homeopathic practice, not accepted medical evidence. Not FDA evaluated.

WARNINGS

Severe or persistent symptoms may be serious. Consult a doctor promptly. Keep out of the reach of children. In case of overdose, get medical help or contact a poison control center right away. If pregnant or breastfeeding, ask a healthcare professional before use.

Keep out of the reach of children.

PREGNANCY OR BREAST FEEDING

If pregnant or breastfeeding, ask a healthcare professional before use.

DIRECTIONS

Place drops under tongue 30 minutes before/after meals. Adults and children 12 years and over: Take 10 drops up to 3 times per day. Consult a physician for use in children under 12 years of age.

OTHER INFORMATION

Tamper resistant. If seal is broken, do not use. After opening, close container tightly and store at room temperature away from heat.

INACTIVE INGREDIENTS

20% ethanol, purified water.

LABEL

Est 1985

Professional Formulas

Complementary Health

Uterine Formula

Homeopathic Remedy

2 FL. OZ. (59 mL)